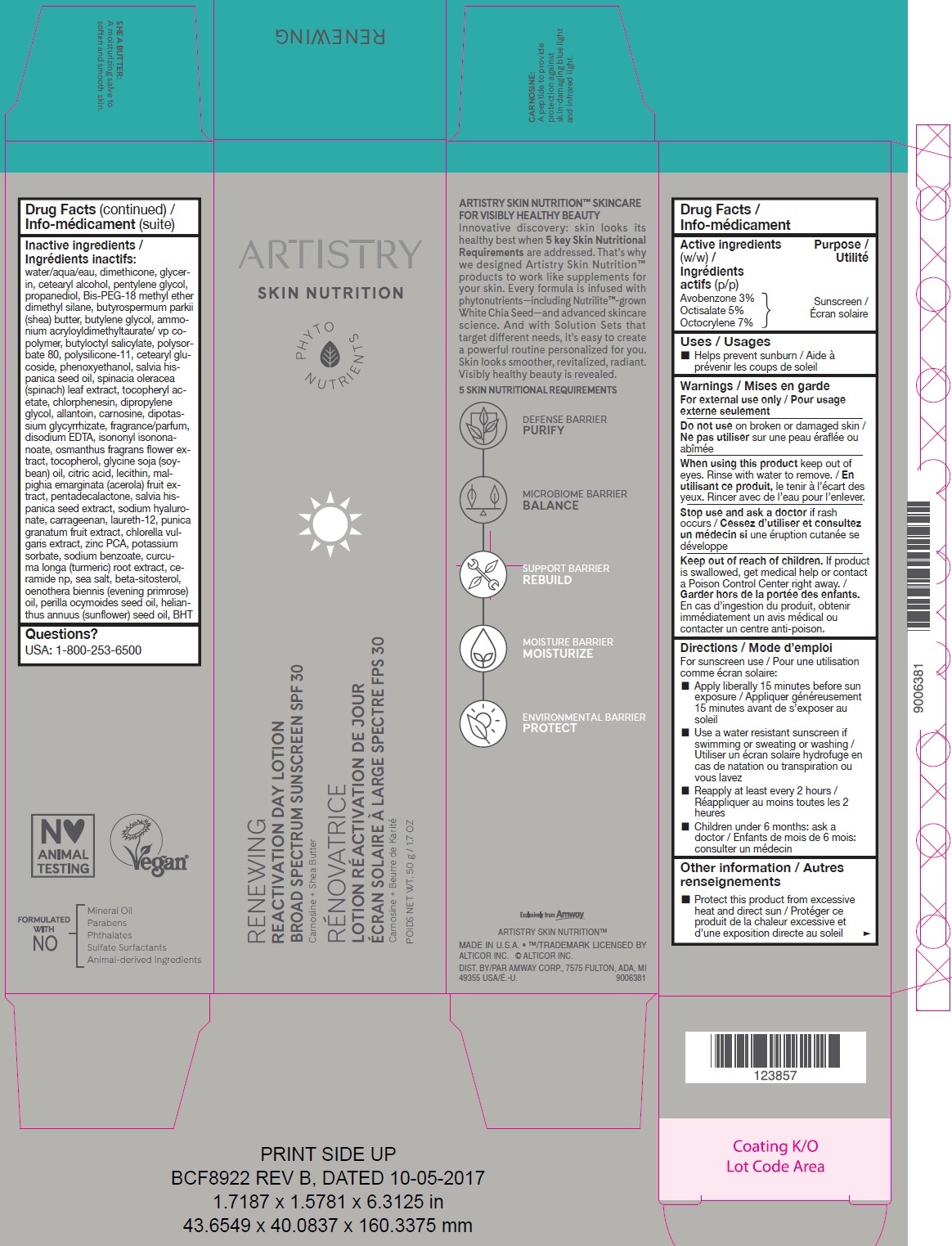 DRUG LABEL: Artistry Skin Nutrition RENEWING Reactivation Day SPF 30
NDC: 10056-051 | Form: LOTION
Manufacturer: Access Business Group LLC
Category: otc | Type: HUMAN OTC DRUG LABEL
Date: 20231021

ACTIVE INGREDIENTS: AVOBENZONE 30 mg/1 g; OCTISALATE 50 mg/1 g; OCTOCRYLENE 70 mg/1 g
INACTIVE INGREDIENTS: WATER; DIMETHICONE; GLYCERIN; CETOSTEARYL ALCOHOL; PENTYLENE GLYCOL; PROPANEDIOL; BIS-PEG-18 METHYL ETHER DIMETHYL SILANE; SHEA BUTTER; BUTYLENE GLYCOL; AMMONIUM ACRYLOYLDIMETHYLTAURATE/VP COPOLYMER; BUTYLOCTYL SALICYLATE; POLYSORBATE 80; DIMETHICONE/VINYL DIMETHICONE CROSSPOLYMER (SOFT PARTICLE); CETEARYL GLUCOSIDE; PHENOXYETHANOL; CHIA SEED OIL; SPINACH; .ALPHA.-TOCOPHEROL ACETATE; CHLORPHENESIN; DIPROPYLENE GLYCOL; ALLANTOIN; CARNOSINE; GLYCYRRHIZINATE DIPOTASSIUM; EDETATE DISODIUM ANHYDROUS; ISONONYL ISONONANOATE; OSMANTHUS FRAGRANS FLOWER; TOCOPHEROL; SOYBEAN OIL; CITRIC ACID MONOHYDRATE; ACEROLA; PENTADECALACTONE; CHIA SEED; HYALURONATE SODIUM; CARRAGEENAN; LAURETH-12; POMEGRANATE; CHLORELLA VULGARIS; ZINC PIDOLATE; POTASSIUM SORBATE; SODIUM BENZOATE; TURMERIC; CERAMIDE NP; SEA SALT; .BETA.-SITOSTEROL; EVENING PRIMROSE OIL; PERILLA FRUTESCENS SEED OIL; SUNFLOWER OIL; BUTYLATED HYDROXYTOLUENE

Artistry Skin Nutrition RENEWING Reactivation Day Lotion SPF 30

Active ingredients (w/w)

Avobenzone 3% Octisalate 5% Octocrylene 7%

Purpose

Sunscreen

Uses

- Helps prevent sunburn

Warnings

For external use only

Do not use

on broken or damaged skin

When using this product

keep out of eyes. Rinse with water to remove.

Stop use and ask a doctor

if rash occurs

Keep out of reach of children.

If product is swallowed, get medical help or contact a Poison Control Center right away.

Directions

For sunscreen use

- Apply liberally 15 minutes before sun exposure
- Use a water resistant sunscreen if swimming or sweating or washing
- Reapply at least every 2 hours
- Children under 6 months: ask a doctor

Other information

- Protect this product from excessive heat and direct sun

Inactive ingredients

water/aqua/eau, dimethicone, glycerin, cetearyl alcohol, pentylene glycol, propanediol, Bis-PEG-18 methyl ether dimethyl silane, butyrospermum parkii (shea) butter, butylene glycol, ammonium acryloyldimethyltaurate/ vp copolymer, butyloctyl salicylate, polysorbate 80, polysilicone-11, cetearyl glucoside, phenoxyethanol, salvia hispanica seed oil, spinacia oleracea (spinach) leaf extract, tocopheryl acetate, chlorphenesin, dipropylene glycol, allantoin, carnosine, dipotassium glycyrrhizate, fragrance/parfum, disodium EDTA, isononyl isononanoate, osmanthus fragrans flower extract, tocopherol, glycine soja (soybean) oil, citric acid, lecithin, malpighia emarginata (acerola) fruit extract, pentadecalactone, salvia hispanica seed extract, sodium hyaluronate, carrageenan, laureth-12, punica granatum fruit extract, chlorella vulgaris extract, zinc PCA, potassium sorbate, sodium benzoate, curcuma longa (turmeric) root extract, ceramide np, sea salt, beta-sitosterol, oenothera biennis (evening primrose) oil, perilla ocymoides seed oil, helianthus annuus (sunflower) seed oil, BHT

Questions?

USA: 1-800-253-6500